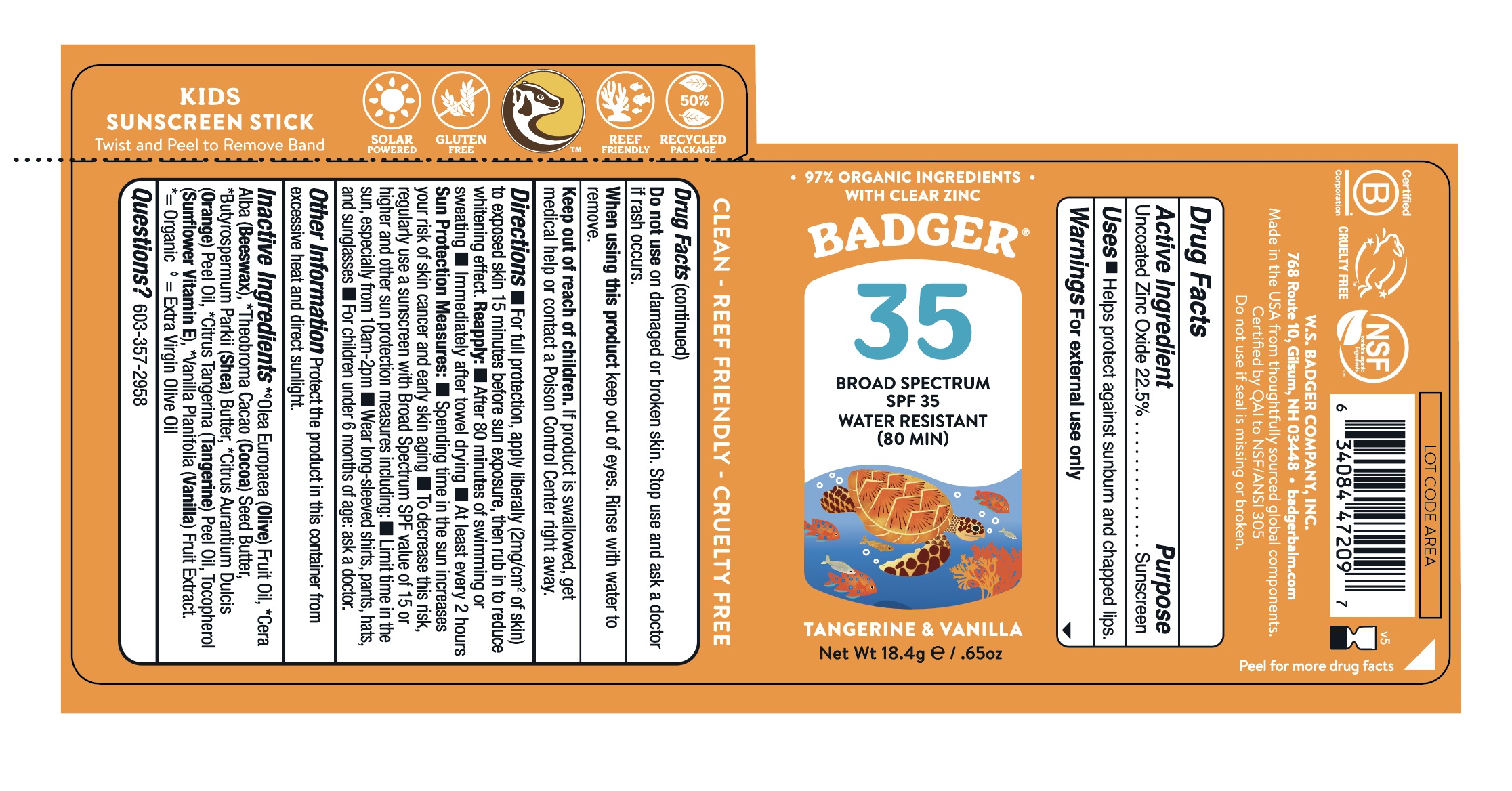 DRUG LABEL: Badger SPF 35 Kids Clear Face Stick
NDC: 62206-3522 | Form: STICK
Manufacturer: W.S. Badger Company, Inc.
Category: otc | Type: HUMAN OTC DRUG LABEL
Date: 20241231

ACTIVE INGREDIENTS: ZINC OXIDE 22.5 g/100 g
INACTIVE INGREDIENTS: OLIVE OIL; COCOA BUTTER; SHEA BUTTER; TOCOPHEROL; ORANGE OIL; MANDARIN OIL; VANILLA; YELLOW WAX

Badger® SPF 35 Kids Clear Face Stick

Drug Facts

Active Ingredient

Non-Nano Uncoated Zinc Oxide 22.5%

Purpose

Sunscreen

Uses

- Helps prevent sunburn and chapped lips
- If used as directed with other sun protection measures (see Directions), decreases the risk of skin cancer and early skin aging caused by the sun.

Warnings

For external use only

Do not use on damaged or broken skin. Stop use and ask a doctor if rash occurs.

When using this product keep out of eyes. Rinse with water to remove.

Keep out of reach of children. If product is swallowed, get medical help or contact a Poison Control Center right away.

Directions

- For full protection, apply liberally (2mg/cm^2 of skin) to exposed skin 15 minutes before sun exposure, then rub in to reduce whitening effect.

Reapply:

- After 80 minutes of swimming or sweating
- Immediately after towel drying
- At least every 2 hours

Sun Protection Measures:

- Spending time in the sun increases your risk of skin cancer and early skin aging
- To decrease this risk, regularly use a sunscreen with Broad Spectrum SPF value of 15 or higher and other sun protection measures including:
  - Limit time in the sun, especially from 10am-2pm
  - Wear long-sleeved shirts, pants, hats, and sunglasses
- For children under 6 months of age: ask a doctor.

Ingredients

[= Certified Organic. 2 - = Extra Virgin Olive Oil.] Olea Europaea (Olive) Fruit Oil, Cera Alba (Beeswax), Theobroma Cacao (Cocoa) Seed Butter, Butyrospermum Parkii (Shea) Butter, Citrus Aurantium Dulcis (Sweet Orange) Peel Oil, Citrus Tangerina (Tangerine) Peel Oil, Tocopherol (Sunflower Vitamin E), Vanilla Planifolia (Vanilla) Fruit Extract.

Other Information

Store at temperatures below 90ºF.

Questions?

603-357-2958

PRINCIPAL DISPLAY PANEL - 18.4 g Applicator Box

Clear Sport SPF 35

BADGER®

Kids

Tangerine & Vanilla

Broad Spectrum

SPF 35

Natural Mineral

All Season Face Stick

Water Resistant 80min

NON GMO
CLEAR ZINC

REEF FRIENDLY

97% ORGANIC INGREDIENTS & CLEAR ZINC OXIDE

ingredients

Net Wt 18.4g/.65oz